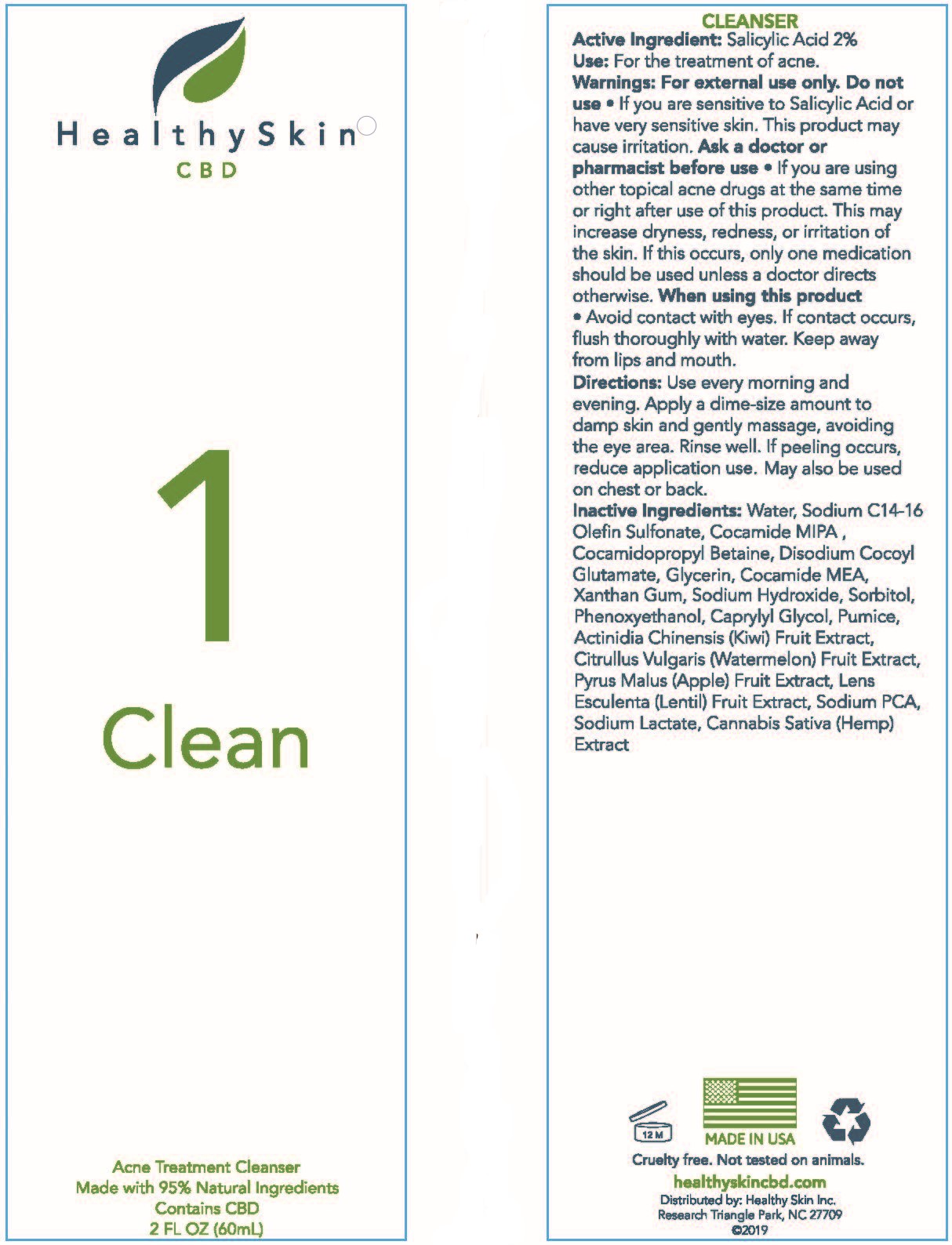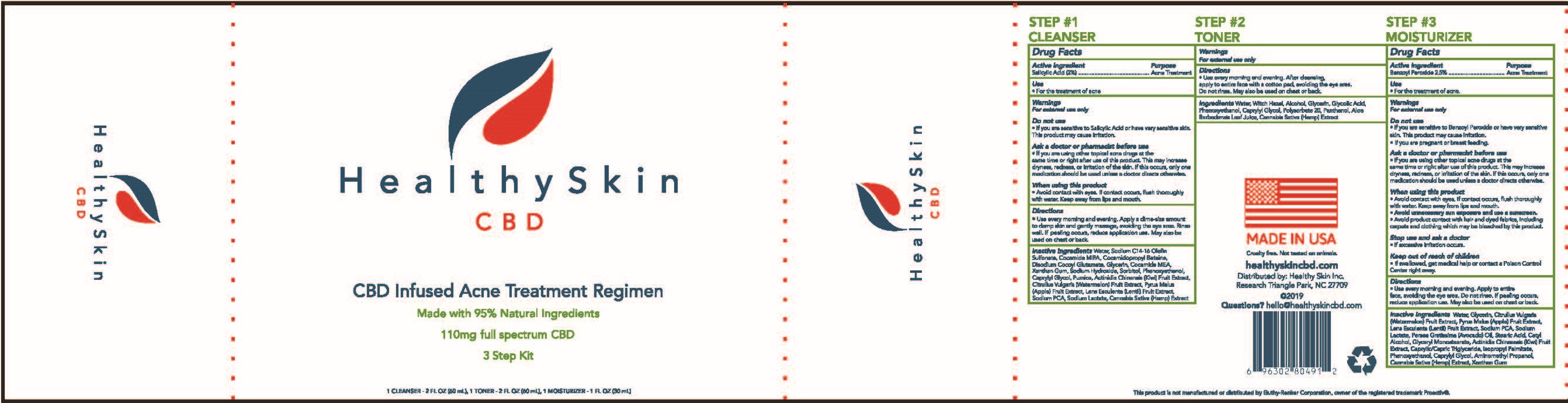 DRUG LABEL: Healthy Skin Cleanser
NDC: 52261-3800 | Form: LIQUID
Manufacturer: Cosco International, Inc.
Category: otc | Type: HUMAN OTC DRUG LABEL
Date: 20200326

ACTIVE INGREDIENTS: SALICYLIC ACID 0.02 kg/1 kg
INACTIVE INGREDIENTS: XANTHAN GUM; COCO MONOETHANOLAMIDE; SORBITOL; GLYCERIN; WATER; PHENOXYETHANOL; CAPRYLYL GLYCOL; SODIUM HYDROXIDE; DISODIUM COCOYL GLUTAMATE; PUMICE; MEDIUM-CHAIN TRIGLYCERIDES; CANNABIDIOL; WATERMELON; APPLE; LENS CULINARIS FRUIT; SODIUM LACTATE; SODIUM PYRROLIDONE CARBOXYLATE; COCAMIDOPROPYL BETAINE; SODIUM C14-16 OLEFIN SULFONATE; COCO MONOISOPROPANOLAMIDE; SODIUM CHLORIDE; KIWI FRUIT; ETHYLHEXYLGLYCERIN; SORBIC ACID

Healthy Skin Cleanser

Drug Facts

Active Ingredient Purpose

Salicylic Acid (2%)......................Acne Treatment

Use

- For the treatment of acne

Warnings

For externatl use only

Do not use

- If you are sensitive to Salicylic Acid or have very sensitive skin.

This product may cause irritation.

Ask a doctor or pharmacist before use

- If you are using other topical acne drugs at the same time or right after use of this product. This may increase dryness, redness, or ittitation of the skin. If this occurs, only one medication should be used unless a doctor directs otherwise.

When using this product

- Avoid contact with eyes. If contact occurs, flush thoroughly with water. Keep away from lips and mouth.

Keep out of reach of children

- If swallowed, get medical help or contact a Poison Control Center right away.

Directions

- Use every morning and evening. Apply a dime-sized amount to damp skin and gently massage, avoiding the eye area. Rinse well. If peeling occurs, reduce application use. May also be used on chest or back.

INACTIVE INGREDIENT

Inactive Ingredients Actinidia Chinensis (Kiwi) Fruit Extract, Cannabidiol, Caprylyl Glycol, Citrullus Lanatis (Watermelon) Fruit Extract, Cocamide MEA, Cocamide MIPA, Cocamidopropyl Betaine, Disodium Cocoyl Glutamate, Ethylhexylglycerin, Glycerin, Lens Esculenta (Lentil) Fruit Extract, Medium-Chain Triglycerides, Phenoxyethanol, Pumice, Pyrus Malus (Apple) Fruit Extract, Sodium C14-16 Olefin Sulfonate, Sodium Chloride, Sodium Hydroxide, Sodium Lactate, Sodium Pyrrolidone Carboxylate, Sorbic Acid, Sorbitol, Water, Xanthan Gum

Questions? hello@healthyskincbd.com